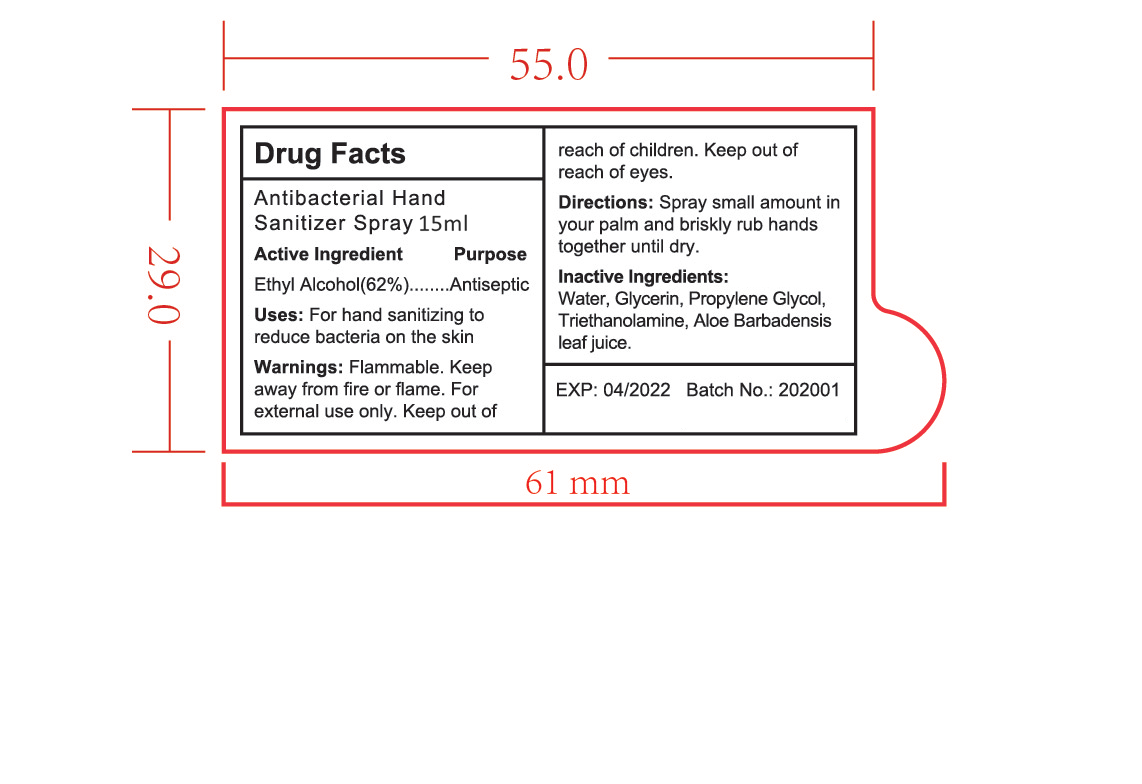 DRUG LABEL: Antibacterial Hand SanitizerSpray
NDC: 47993-312 | Form: GEL
Manufacturer: NINGBO JIANGBEI OCEAN STAR TRADING CO.,LTD
Category: otc | Type: HUMAN OTC DRUG LABEL
Date: 20201105

ACTIVE INGREDIENTS: ALCOHOL 62 g/112 mL
INACTIVE INGREDIENTS: GLYCERIN; WATER; PROPYLENE GLYCOL; TRIETHANOLAMINE BENZOATE; ALOE VERA LEAF

47993-312

Active ingredients

Ethyl Alcohol(62%)

PURPOSE

Antiseptic

Uses：

For hand sanitizing to reduce bacteria on the skin.

Warnings:

Flammable: Keep away from high heat or flames.For external use only.

Keep out of reach of children.

WHEN USING

keep out of reach of eyes.

Directions:

Spray small amount in your palm and briskly rub hands together until dry.

Inactive Ingredients:

Water, Glycerin, Propylene Glycol, Triethanolamine, Aloe Barbadensis leaf juice.